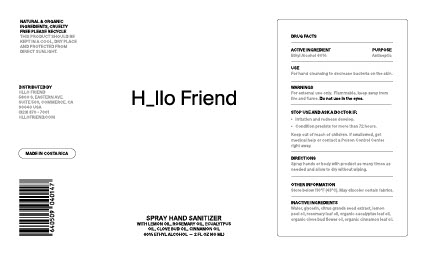 DRUG LABEL: Hand Sanitizer
NDC: 80751-400 | Form: SPRAY
Manufacturer: Aromas Para El Alma S.A.
Category: otc | Type: HUMAN OTC DRUG LABEL
Date: 20220106

ACTIVE INGREDIENTS: ALCOHOL 60 mL/100 mL
INACTIVE INGREDIENTS: LEMON OIL; ROSEMARY; CINNAMON OIL; CITRUS FRUIT; GLYCERIN; WATER; CLOVE LEAF OIL; EUCALYPTUS GLOBULUS LEAF

Spray Hand Sanitizer - 60 ml

PURPOSE

Antiseptic

Warnings

For external use only. Flammable, Keep away from fire and flame.

Do not use in the eyes

- Do not use in the eyes

Stop Use and Ask a Doctor If:

- irritation and redness develop.

- Condition persists for more than 72 hours.

DIRECTIONS

- Spray hands or body with product as many times as needed and allow to dry without wiping

Other information

- Store below 110 F (43C) . May Discolor certain fabrics

Active Ingredient

Ethyl Alcohol 60%

Stop USe and Ask Doctor if

Stop use and ask a doctor if:

- rritation and redness develop.

- Condition persists for more than 72 hours.

KEEP OUT OF REACH OF CHILDREN. IF SWALLOWED, GET MEDICAL HELP OR CONTACT A POISON CONTROL CENTER RIGHT AWAY

USE

For hand cleansing to decrease bacteria on the skin

Inactive Ingredients

Water, glycerin, citrus grands seed extract, lemon peel oil, rosemary leaf oil, organic eucalyptus leaf oil, organic clove bud flower oil, organic cinnamon leaf oil

Package Label

2 FL OZ (60 ml) NDC: 80751-400-02